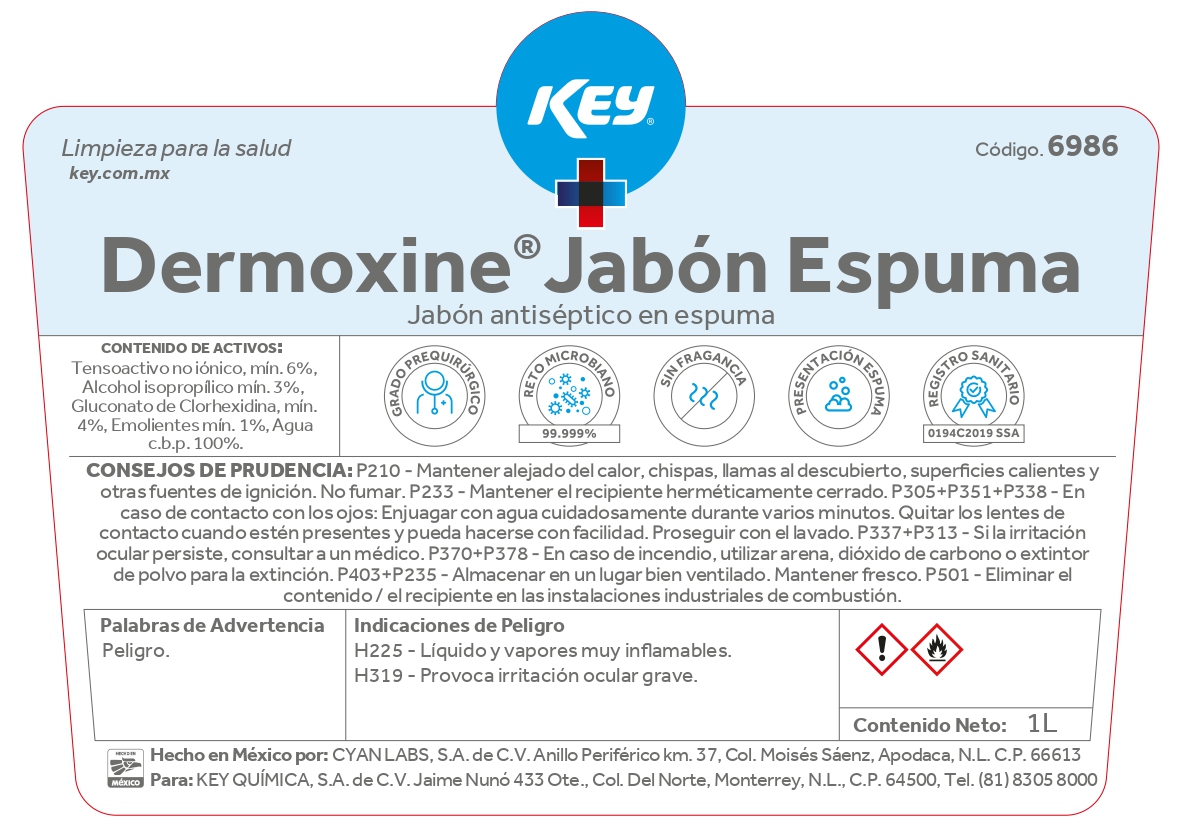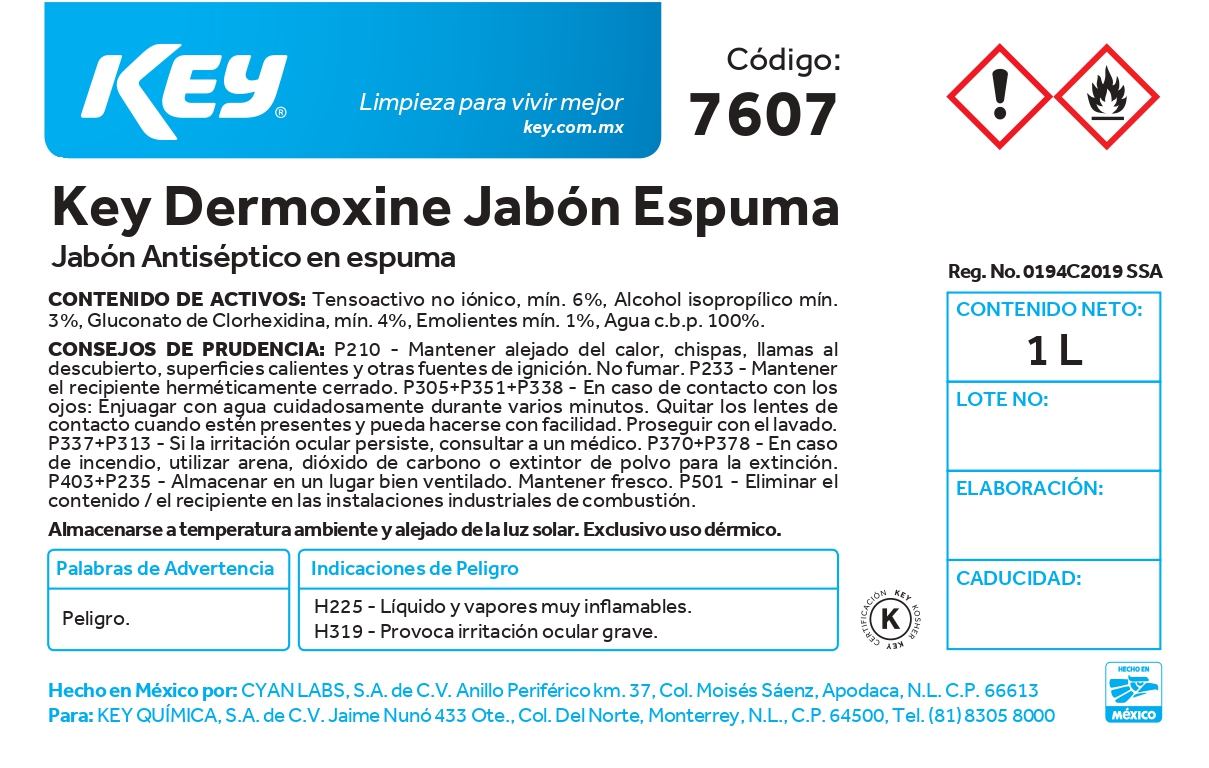 DRUG LABEL: Key Dermoxine Jabon Espuma
NDC: 58345-104 | Form: LIQUID
Manufacturer: Key Química S.A. de C.V.
Category: otc | Type: HUMAN OTC DRUG LABEL
Date: 20250107

ACTIVE INGREDIENTS: CHLORHEXIDINE GLUCONATE 4.2 g/100 mL
INACTIVE INGREDIENTS: POLYQUATERNIUM-7 (70/30 ACRYLAMIDE/DADMAC; 2600000 MW); WATER; ISOPROPYL ALCOHOL; COCAMINE OXIDE; GLYCERIN

58345-104

Active Ingredients

Gluconato de Clorhexidina 4 %

Purpose

Antiseptic

Use

To decrease bacteria on skin that could cause diseases. Recommend for repeated use.

Warnings

Flammable, keep away from fire or flame. For external use only.

Do not use this product in or near the eyes.

Stop use

Stop use if irritation or redness develop. If conditions persist for more than 72 hours, consult a doctor.

Keep out of reach of children. If swallowed, seek inmediate medical attention or call a poison control center.

Directions

Wet hands thoroughly with product and rinse after.

Innactive ingredients

Water (aqua), Isopropyl Alcohol, Cocamine Oxide, Glycerin and Polyquaternium-7.

Package Label - Principal Display Panel

Key Demorxine Jabón Espuma